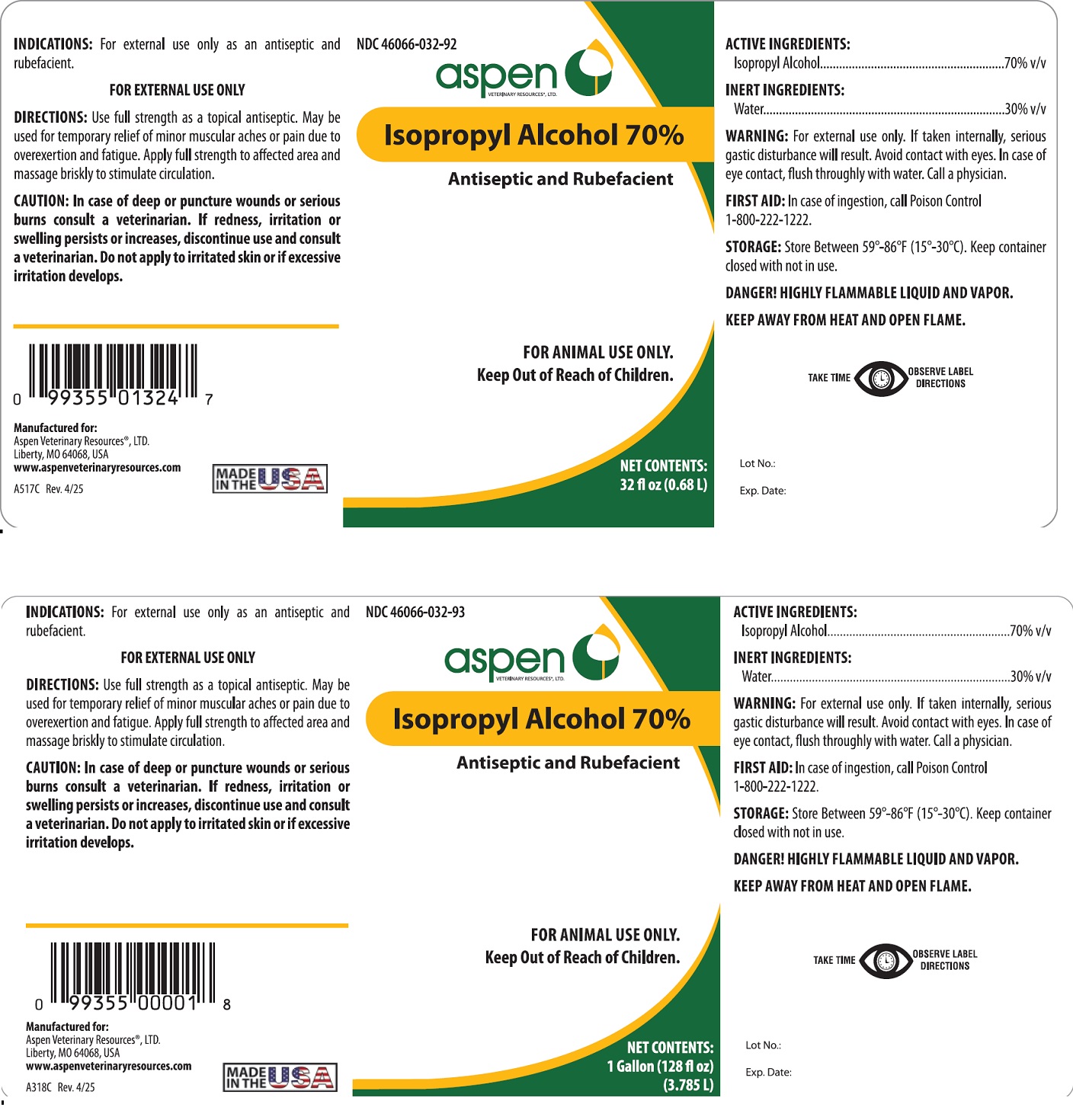 DRUG LABEL: Isopropyl Alcohol
NDC: 46066-032 | Form: SOLUTION
Manufacturer: Aspen Veterinary
Category: animal | Type: OTC ANIMAL DRUG LABEL
Date: 20250415

ACTIVE INGREDIENTS: ISOPROPYL ALCOHOL 0.70 mL/1 mL
INACTIVE INGREDIENTS: WATER 0.30 mL/1 mL

WARNINGS AND PRECAUTIONS

Isopropyl Alcohol 70%

Antiseptic and Rubefacient

FOR ANIMAL USE ONLY

FOR EXTERNAL USE ONLY

Keep Out of Reach of Children

ACTIVE INGREDIENTS:

Isopropyl Alcohol ............................ 70%v/v

INACTIVE INGREDIENTS:

Water ........................................... 30%v/v

INDICATIONS: For external use only as an antiseptic and rubefacient.

WARNING: For external use only. If taken internally, serious gastric disturbance will result. Avoid contact with eyes. In case of eye contact, flush throughly with water. Call a physician.

FIRST AID: In case of ingestion, call Poison Control 1-800-222-1222.

STORAGE: Store Between 59°-86°F (15°-30°C). Keep container closed with not in use.

DANGER! HIGHLY FLAMMABLE LIQUID AND VAPOR.

KEEP AWAY FROM HEAT AND OPEN FLAME

DIRECTIONS: Use full strength as topical antiseptic. May be used for temporary relief of minor muscular aches or pain due to overexertion and fatigue. Apply full strength to affected area and massage briskly to stimulate circulation.

CAUTION: In case of deep or puncture wounds or serious burns, consult a veterinarian. If redness, irritation, or swelling persists or increases, discontinue use and consult a veterinarian. Do not apply to irritated skin or if excessive irritation develops.

Manufactured for:

Aspen Veterinary Resources, Ltd.

Liberty, MO 64068, USA

FC143C

Made in the USA.

Rev. 4/25